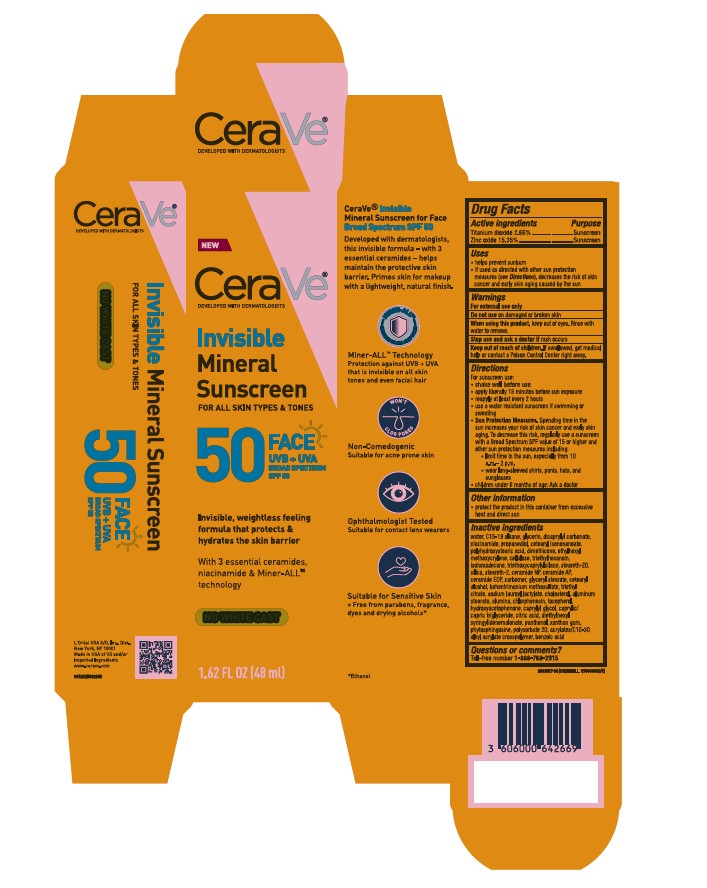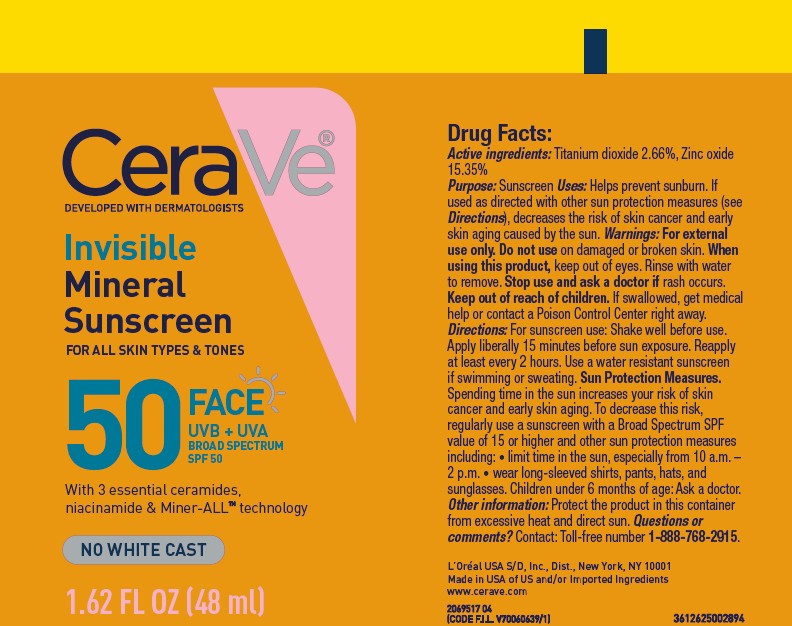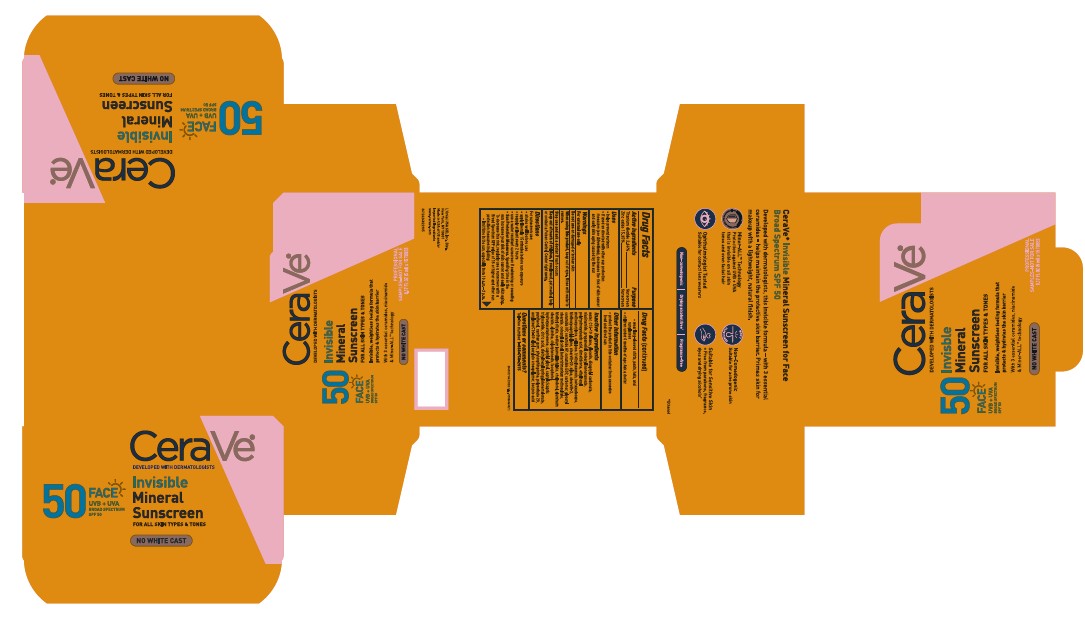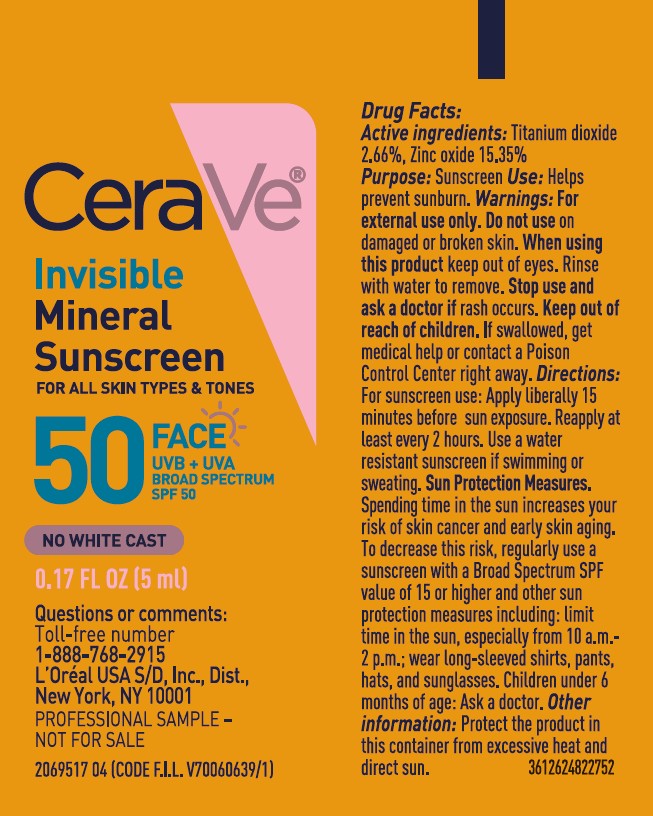 DRUG LABEL: CERAVE DEVELOPED WITH DERMOTOLOGISTS Invisible Mineral Sunscreen FOR ALL SKIN TYPES AND TONES FACE UVB AND UVA BROAD SPECTRUM SPF 50
NDC: 82046-894 | Form: LOTION
Manufacturer: L’Oreal USA Products Inc
Category: otc | Type: HUMAN OTC DRUG LABEL
Date: 20251114

ACTIVE INGREDIENTS: TITANIUM DIOXIDE 26.6 mg/1 mL; ZINC OXIDE 153.5 mg/1 mL
INACTIVE INGREDIENTS: WATER; C15-19 ALKANE; GLYCERIN; DICAPRYLYL CARBONATE; NIACINAMIDE; PROPANEDIOL; CETEARYL ISONONANOATE; POLYHYDROXYSTEARIC ACID (2300 MW); DIMETHICONE; ETHYLHEXYL METHOXYCRYLENE; POWDERED CELLULOSE; TRIETHYLHEXANOIN; ISOHEXADECANE; TRIETHOXYCAPRYLYLSILANE; STEARETH-20; SILICA; STEARETH-2; CERAMIDE NP; CERAMIDE AP; CERAMIDE 1; CARBOMER; GLYCERYL STEARATE; CETEARYL ALCOHOL; BEHENTRIMONIUM METHOSULFATE; TRIETHYL CITRATE; SODIUM LAUROYL LACTYLATE; CHOLESTEROL; ALUMINUM STEARATE; ALUMINA; CHLORPHENESIN; TOCOPHEROL; HYDROXYACETOPHENONE; CAPRYLYL GLYCOL; CAPRYLIC/CAPRIC TRIGLYCERIDE; CITRIC ACID; DIETHYLHEXYL SYRINGYLIDENEMALONATE; PANTHENOL; XANTHAN GUM; PHYTOSPHINGOSINE; POLYSORBATE 20; ACRYLATES/C10-30 ALKYL ACRYLATE CROSSPOLYMER (60000 MPA.S); BENZOIC ACID

Drug Facts

Active ingredients

Titanium dioxide 2.66%

Zinc oxide 15.35%

Purpose

Sunscreen

Use

- helps prevent sunburn
- if used as directed with other sun protection measures (see Directions), decreases the risk of skin cancer and early skin aging caused by the sun

Warnings

For external use only

Do not use

on damaged or broken skin.

When using this product,

keep out of eyes. Rinse with water to remove.

Stop use and ask a doctor if

rash occurs

Keep out of reach of children

If swallowed, get medical help or contact a Poison Control Center right away.

Directions

For sunscreen use:

- shake well before use
- apply liberally 15 minutes before sun exposure
- reapply at least every 2 hours
- use a water resistant sunscreen if swimming or sweating
- Sun Protection Measures. Spending time in the sun increases your risk of skin cancer and early skin aging. To decrease this risk, regularly use a sunscreen with a Broad Spectrum SPF value of 15 or higher and other sun protection measures including:
- limit time in the sun, especially from 10 a.m. - 2 p.m.
- wear long-sleeved shirts, pants, hats, and sunglasses
- children under 6 months of age: Ask a doctor

Other information

- protect the product in this container from excessive heat and direct sun

Inactive ingredients

water, C15-19 allkane, glycerin, dicaprylyl carbonate, niacinamide, propanediol, cetearyl isononanoate, polyhydroxystearic acid, dimethicone, ethylhexyl methoxycrylene, cellulose, triethylhexanoin, isohexadecane, triethoxycaprylylsilane, steareth-20, silica, steareth-2, ceramide NP, ceramide AP, ceramide EOP, carbomer, glyceryl stearate, cetearyl alcohol, behentrimonium methosulfate, triethyl citrate, sodium lauroyl lactylate, cholesterol, aluminum stearate, alumina, chlorphenesin, tocopherol, hydroxyacetophenone, caprylyl glycol, caprylic/capric triglyceride, citric acid, diethylhexyl syringylidenemalonate, panthenol, xanthan gum, phytosphingosine, polysorbate 20, acrylates/C10-30 alkyl acrylate crosspolymer, benzoic acid

Questions or comments?

Toll-free number 1-888-768-2915